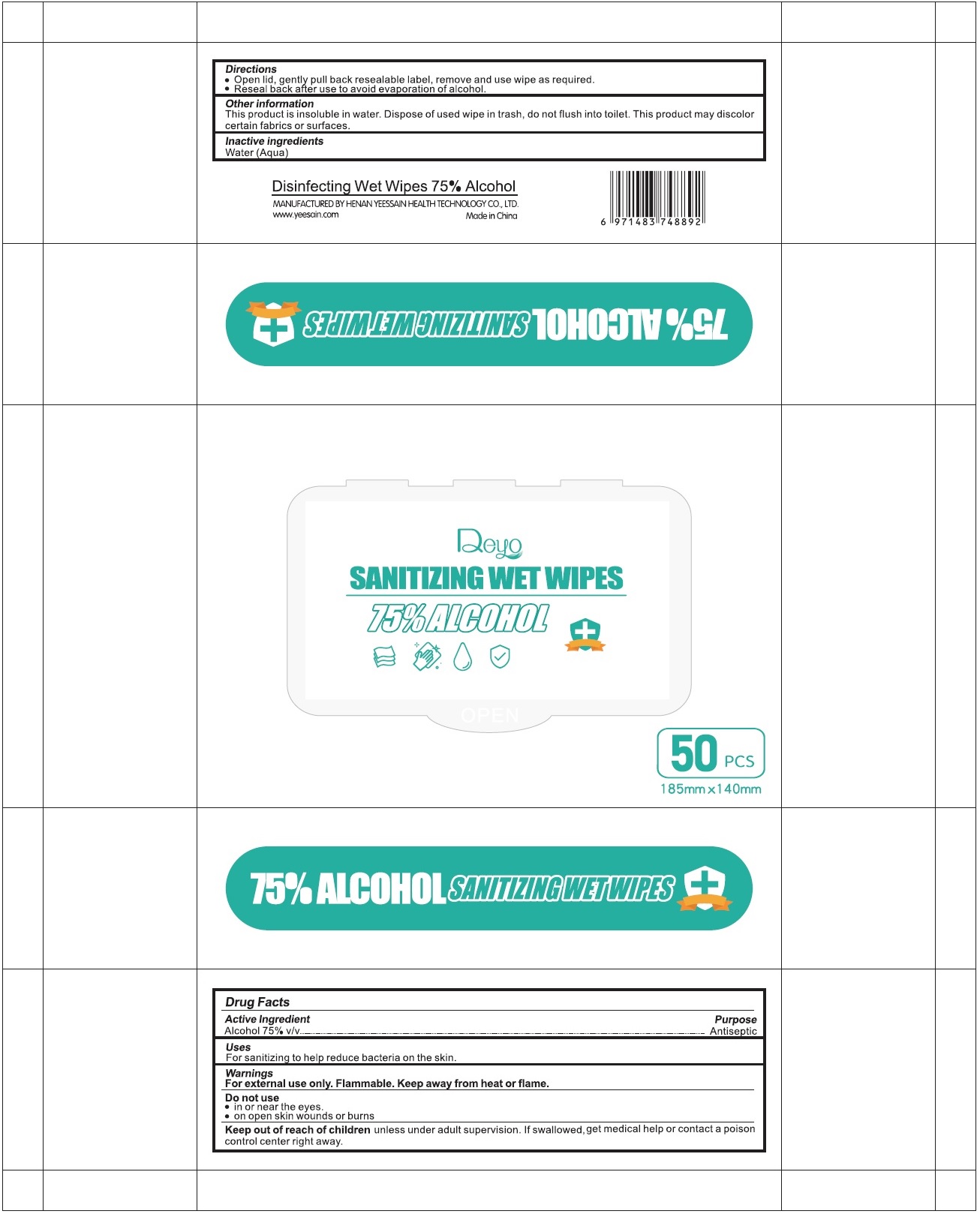 DRUG LABEL: The Nordic Shield Sanitizer Wipes
NDC: 79232-900 | Form: CLOTH
Manufacturer: The Nordic Shield Aps
Category: otc | Type: HUMAN OTC DRUG LABEL
Date: 20200909

ACTIVE INGREDIENTS: ALCOHOL 75 mL/100 mL
INACTIVE INGREDIENTS: WATER

Deyo SANITIZING WET WIPES

Active Ingredient

Alcohol 75% v/v

Purpose

Antiseptic

Uses

For sanitizing to help reduce bacteria on the skin.

Warnings

For external use only. Flammable. Keep away from heat or flame.

Do not use

• in or near the eyes.

• on open skin wounds or burns

Keep out of reach of children unless under adult supervision. If swallowed, get medical help or contact a poison control center right away.

Directions

• Open lid, gently pull back resealable label, remove and use wipe as required.

• Reseal back after use to avoid evaporation of alcohol.

Other information

This product is insoluble in water. Dispose of used wipe in trash, do not flush into toilet. This product may discolor certain fabrics or surfaces.

Inactive ingredients

Water (Aqua)

Disinfecting Wet Wipes 75% Alcohol

MANUFACTURED BY HENAN YEESSAIN HEALTH TECHNOLOGY CO. LTD.

www.yeesain.com

Made in China